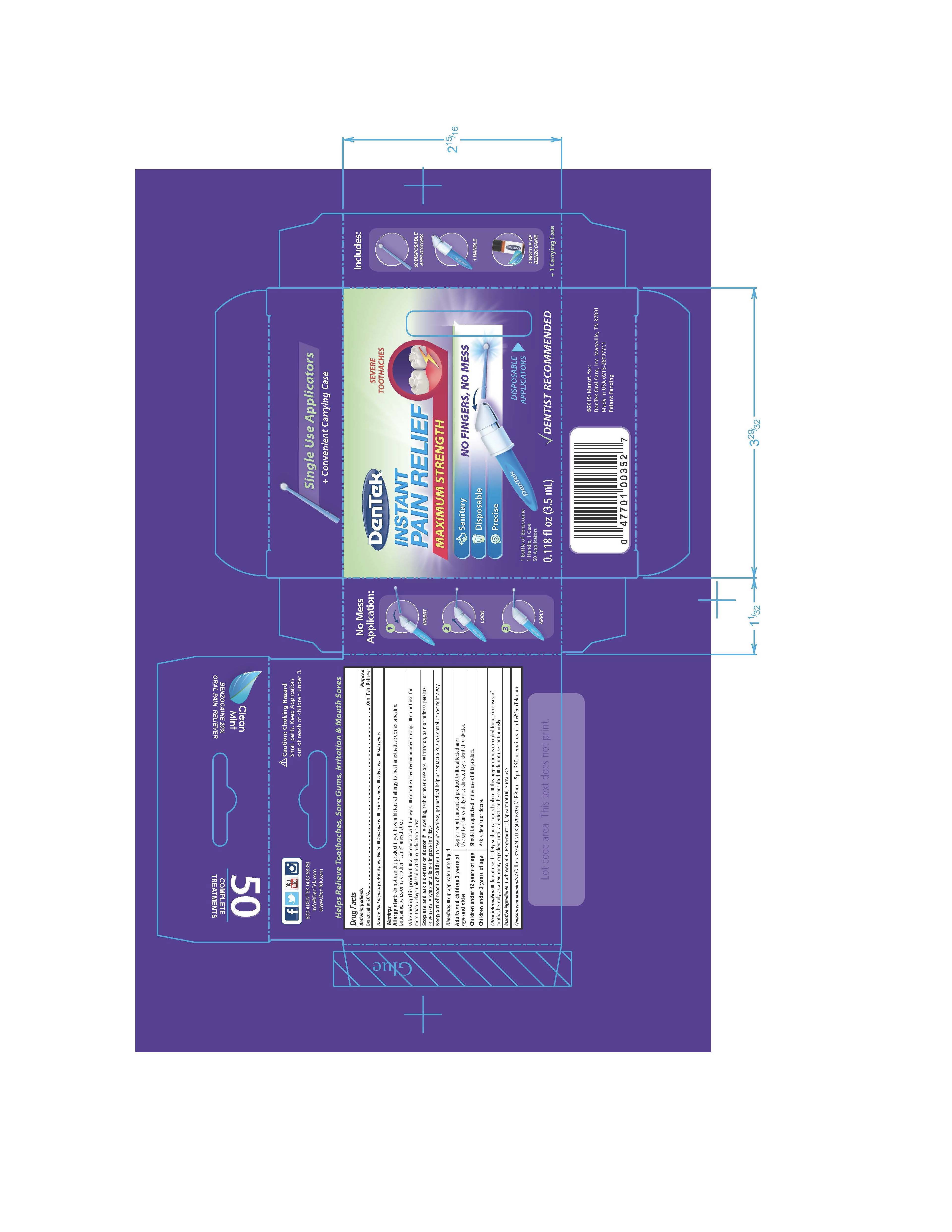 DRUG LABEL: Dentek Instant Pain Relief
NDC: 83062-410 | Form: LIQUID
Manufacturer: IIMED MEDICAL MEXICANA S. DE R.L. DE C.V
Category: otc | Type: HUMAN OTC DRUG LABEL
Date: 20231005

ACTIVE INGREDIENTS: BENZOCAINE 200 mg/1 mL
INACTIVE INGREDIENTS: PEPPERMINT OIL 2.2 mg/1 mL; SUCRALOSE 10 mg/1 mL; SPEARMINT OIL 3.3 mg/1 mL; POLYETHYLENE GLYCOL 400 784.5 mg/1 mL

IIMED Dentek Instant Pain Relief

Active ingredient

Benzocaine 20%

Purpose

Oral Pain Reliever

Uses

for the temporary relief of pain due to:

- toothaches
- canker sore
- cold sores
- sore gums

Warnings

Allergy Alert: do not use this product if you have a history of allery to local anesthetics such as procaine, butacaine, benzocaine or other "caine" anesthetics.

When using this product

- avoid contact with the eyes
- do not exceed recommended dosage
- do not use for more than 7 days unless than directed by a doctor/dentist

Stop use and ask a dentist or doctor if

- swelling, rash or fever develops
- irritation, pain or redness persists or worsens
- symptoms do not improve in 7 days

Keep out of reach of children

In case of overdose, get medical help or contact a Poison Control Center right away.

Directions

dip applicator into liquid

Adults and children 2 years of age and older: Apply a small amount of product to the affected area. Use up to 4 times daily or as directed by a dentist or doctor.

Children under 12 years of age: Should be supervised in the use of this product.

Children under 2 years of age: Ask a dentist or doctor.

Other information

- do not use if safety seal on carton is broken
- this preparation is intended for use in cases of toothache, only as a temporary expedient until a dentist can be consulted
- do not use continuously

Inactive ingredients

Carbowax 400, Peppermint Oil, Spearmint Oil, Sucralose

Questions or comments?

Call us 800-4DENTEK (433-6835) M-F 8am - 5pm EST or email us at info@DenTek.com